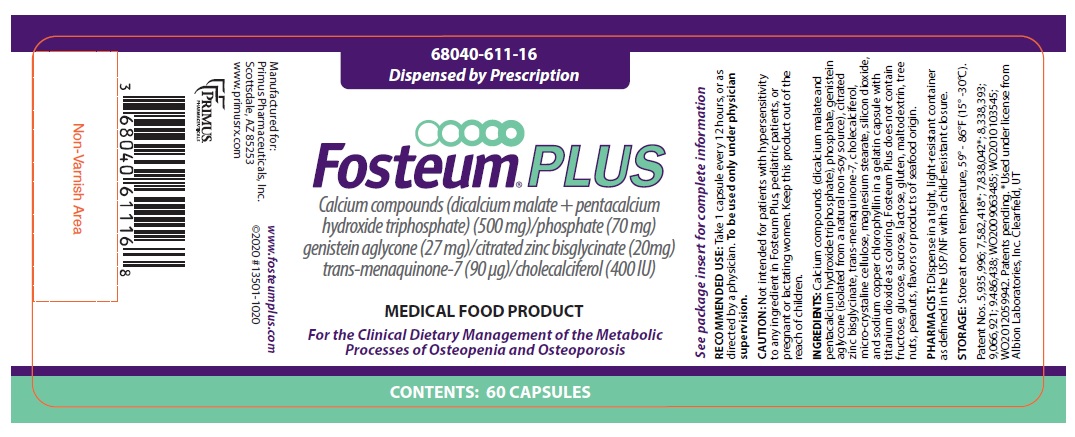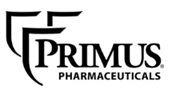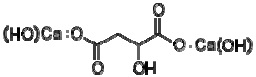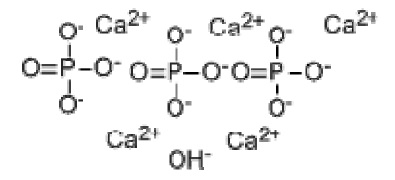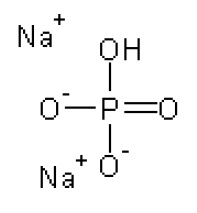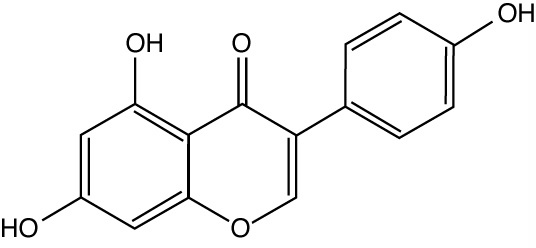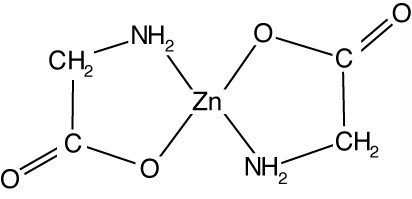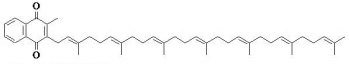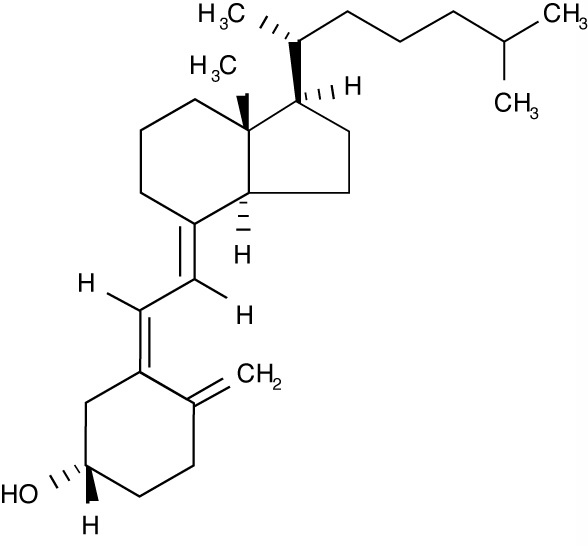 DRUG LABEL: FOSTEUM PLUS
NDC: 68040-611 | Form: CAPSULE
Manufacturer: Primus Pharmaceuticals, Inc.
Category: other | Type: MEDICAL FOOD
Date: 20250303

ACTIVE INGREDIENTS: DICALCIUM MALATE DIHYDROXIDE 200 mg/1 1; TRIBASIC CALCIUM PHOSPHATE 300 mg/1 1; PHOSPHATE ION 70 mg/1 1; GENISTEIN 27 mg/1 1; ZINC GLYCINATE CITRATE 20 mg/1 1; MENAQUINONE 7 90 ug/1 1; CHOLECALCIFEROL 400 [iU]/1 1
INACTIVE INGREDIENTS: GELATIN TYPE B BOVINE (150 BLOOM); TITANIUM DIOXIDE; MICROCRYSTALLINE CELLULOSE; MAGNESIUM STEARATE; SILICON DIOXIDE; SODIUM PHOSPHATE, DIBASIC, ANHYDROUS

FOSTEUM PLUS® Capsules
calcium compounds (dicalcium malate and pentacalcium hydroxide triphosphate) (500 mg)
phosphate (70 mg)
genistein aglycone (27 mg)
citrated zinc bisglycinate (20 mg)
trans-menaquinone-7 (90 μg)
cholecalciferol (400 IU)

Fosteum PLUS® is a specially formulated prescription medical food product for the clinical dietary management of the metabolic processes of osteopenia and osteoporosis. Fosteum PLUS must be administered under physician supervision.

DESCRIPTION

Fosteum PLUS consists of a specially formulated proprietary blend of dicalcium malate and pentacalcium hydroxide triphosphate, sodium phosphate, high purity genistein aglycone from a natural, non-soy source, citrated zinc bisglycinate, trans-menaquinone-7 (vitamin K2), and cholecalciferol (vitamin D3). Genistein aglycone reduces osteoclast activity and stimulates osteoblast activity. Citrated zinc bisglycinate works synergistically with genistein aglycone, while both citrated zinc bisglycinate and vitamin D3 also work independently to promote mineralization activity in bone. Vitamin K2 works with vitamin D3 in aiding bone-building enzymes in the deposition of calcium in bone during remodeling. Vitamin D3 also facilitates calcium absorption from the intestine.

CALCIUM COMPOUNDS

DICALCIUM MALATE

Each Fosteum PLUS capsule contains 200 mg of dicalcium malate for a total daily intake of 400 mg. Dicalcium malate is chemically described as calcium 2,4-dihydroxy-4-oxobutanoate. The formula for dicalcium malate is Ca2C4H6O7; its molecular weight is 246.2. The structural formula is:

PENTACALCIUM HYDROXIDE TRIPHOSPHATE

Each Fosteum PLUS capsule contains 300 mg of pentacalcium hydroxide triphosphate for a total daily intake of 600 mg. The formula for pentacalcium hydroxide triphosphate is (Ca5(OH)(PO4)3); its molecular weight is 502.31. The structural formula is:

PHOSPHATE

Each Fosteum PLUS capsule contains 70 mg of phosphate for a total daily intake of 140 mg phosphate. Twenty-three (23) mg comes from sodium phosphate dibasic and 47 mg comes from pentacalcium hydroxide triphosphate (see above for structural formula). The empirical formula for sodium phosphate dibasic is Na2HPO4; its molecular weight is 141.96. The structural formula is:

GENISTEIN AGLYCONE

Each Fosteum PLUS capsule contains 27 mg of genistein aglycone (genistein), isolated from a botanical non-soy source, for a total daily intake of 54 mg. In clinical trials, this level of intake was shown to increase bone mineral density (BMD). Genistein is chemically described as 4’,5,7-trihydroxyisoflavone or 5,7-dihydroxy-3-(4-hydroxyphenyl)-4H-1-benzopyran-4-one. It is the aglycone form of the glucoside isoflavone molecule genistein. The formula of genistein is C15H10O5: The molecular weight is 270.2. The structural formula is:

CITRATED ZINC BISGLYCINATE

Each Fosteum PLUS capsule contains 20 mg citrated zinc bisglycinate, a glycine amino acid chelate of zinc, formed in the presence of citric acid that provides approximately 4 mg of elemental zinc per capsule. Zinc is an essential mineral co-factor required by enzymes involved in bone metabolism and has important physiological functions in other tissues throughout the body. Elemental zinc has also been shown to have synergistic effects with genistein on bone formation. This zinc bisglycinate, formed in the presence of citric acid, has been shown to have improved absorption over inorganic zinc salts, such as zinc sulfate. Zinc bisglycinate, a chelate of zinc, is complex with an empirical formula of C4H8O4Zn; its molecular weight is 215.5. The structural formula is:

When generated in the presence of citric acid, citrate and glycinate ions (not shown) participate in this structure, forming citrated zinc bisglycinate, contributing to the complexity of the molecule.

TRANS-MENAQUINONE-7

Each Fosteum PLUS capsule contains 90 μg of vitamin K2 as pure trans-menaquinone-7 crystals for a total daily intake of 180 μg. Vitamin K2 is chemically described as2-[(2E,6E,10E,14E,18E,22E) -3,7,11,15,19,23,27-hepta-methyloctacosa-2,6,10,14,18,22,26-heptaenyl]-3-methylnaphthalene-1,4-dione (IUPAC convention) The formula for menaquinone-7 is C46H64O2; its molecular weight is 649.0. The structural formula is:

CHOLECALCIFEROL

Each Fosteum PLUS capsule contains cholecalciferol equivalent to 400 IU vitamin D3. Vitamin D3 is the natural form of the vitamin produced when skin is exposed to the sun. Vitamin D3 is necessary for proper absorption of calcium from the intestine and the use of absorbed calcium in the mineralization of bone. Cholecalciferol is the natural precursor of calcitriol (1,25-dihydroxy-cholecalciferol), the physiologically active form of vitamin D. It is described as (3ßμ,5Z,7E)-9,10-secocholesta-5,7, 10(19)-triene-3-ol. The empirical formula is C27H44O; its molecular weight is 384.6. The structural formula is:

OTHER INGREDIENTS

Fosteum PLUS contains the following other ingredients as excipients: micro-crystalline cellulose, magnesium stearate, and silicon dioxide. The capsule is bovine gelatin, with titanium dioxide and sodium copper chlorophyllin for the capsule color. Fosteum PLUS does not contain fructose, glucose, sucrose, lactose, gluten, maltodextrin, tree nuts, peanuts, soy, flavors or products of seafood origin.

MEDICAL FOOD

Medical Food products are used under a physician’s supervision for the dietary management of diseases in patients with particular medical or metabolic needs due to their disease or condition. The U.S. Congress defined “medical food” in the Orphan Drug Act and Amendments of 1988 as “a food which is formulated to be consumed or administered enterally under the supervision of a physician, and which is intended for the specific dietary management of a disease or condition for which distinctive nutritional requirements, based on recognized scientific principles, are established by medical evaluation.” Fosteum PLUS has been developed, manufactured and labeled in accordance with both the statutory and the FDA regulatory definition of a medical food. Fosteum PLUS is to be used only under a physician’s supervision.

GENERALLY RECOGNIZED AS SAFE

The ingredients in Fosteum PLUS are Generally Recognized As Safe (GRAS). This is the statutory safety standard that the U.S. Food and Drug Administration (FDA) require of all ingredients added to food products. The standard for an ingredient to achieve GRAS status requires technical demonstration of non-toxicity and safety, general recognition of safety through widespread usage and agreement of that safety by experts in the field.

LOW BONE MASS AND OSTEOPOROSIS

Low bone mass (osteopenia) and osteoporosis are gradations of bone loss. Low bone mass may progress to osteoporosis. Low bone mass and osteoporosis occur when the metabolic processes of normal bone turnover are unbalanced in favor of resorption activity. The World Health Organization (WHO) defines low bone mass as a T-score (by dual energy absorption technology, DXA) between -1.0 and -2.5. Osteoporosis is defined at a T-score lower than -2.5.

CLINICAL PHARMACOLOGY

Mechanism of Action

Fosteum PLUS acts by restoring and maintaining the balance of bone turnover toward normal levels in patients with osteopenia and osteoporosis. Calcium and phosphate are necessary for proper bone formation. Preclinical and clinical data suggest that the genistein in Fosteum PLUS reduces osteoclast-mediated bone resorption and stimulates the bone forming activity of osteoblasts. The zinc in Fosteum PLUS acts synergistically with the genistein to retard maturation of osteoclasts and promote the maturation and number of osteoblasts. Menaquinone-7 has been shown to activate osteocalcin by enhancing the replacement of carboxyl groups for glutamic acid residues on osteocalcin thereby increasing
its binding to calcium for proper bone mineralization. Cholecalciferol improves the absorption of calcium and its deposition into the mineral matrix of bone.

Osteopenia and osteoporosis most commonly occur because of hormonal changes associated with the aging process or the use of certain classes of drugs. Bone loss associated with these conditions is primarily due to the metabolic imbalance that occurs when osteoclast activity is greater than osteoblast activity. The imbalance of bone resorption in excess of bone formation is progressive and often leads to fractures. These minimal trauma fractures may lead to significant morbidity and mortality. Clinical dietary management of the metabolic processes underlying osteopenia and osteoporosis helps to restore the balance between bone resorption and bone formation and consequently increases bone mineral density over time.

Calcium and Phosphate

The calcium in Fosteum PLUS is essential for building bone. Calcium is part of the structure of bone in the form of hydroxyapatite (pentacalcium hydroxide triphosphate). Proper bone remodeling requires both calcium and phosphate consumed in the diet. Low phosphate intake even in the presence of adequate calcium consumption has been shown to decrease osteoblast function and increase osteoclast activity resulting in net bone loss or decrease in bone mineral density. New bone mineralization consumes calcium and phosphate at a molar ratio of approximately 1.6:1. Fosteum PLUS contains a molar ratio of calcium to phosphate that approximates this number.

Genistein Aglycone

The genistein in Fosteum PLUS decreases the maturation of osteoclasts and promotes the formation of osteoblasts from progenitor stem cells to increase their number and activity in bone. The net effect is an enhancement of bone formation that restores bone remodeling toward normal levels and results in an increase in BMD over time. More specifically, preclinical studies suggest the following mechanisms of action: Genistein acts to reverse the effects of estrogen loss by decreasing cytokine production and increasing transforming growth factor ß (TGFß) levels. This results in a decrease in receptor activator of nuclear factor kappa B ligand (RANK-L) production, an increase in osteoprotegerin (OPG) levels, and interruption of the interaction between RANK and RANK-L that produces an overall decrease in osteoclast activity. Genistein also increases insulin-like growth factor-1 (IGF-1) leading to an increased number of proto-osteoblasts developed from mesenchymal stem cells. Genistein restores endothelial cell signals resulting in increased recruitment of these precursor cells to form osteoblasts. Genistein also reverses early apoptosis of osteoblasts. These actions likely produce a net increase in osteoblast activity and concomitant decrease in osteoclast activity. In clinical trials, the genistein in Fosteum PLUS decreased urinary levels of the bone resorption markers: urinary and serum collagen type 1 cross-linked C-telopeptide (CTX), deoxypyridinoline (DPYR) and pyridinoline (PYR), and increased serum levels of the bone formation markers: bone-specific alkaline phosphatase (BAP), osteocalcin (OC), and IGF-1.

ZINC (ELEMENTAL)

Zinc has a positive effect on bone formation. The zinc in Fosteum PLUS is the citrated bisglycinate form, which has been shown to have improved absorption from the intestine compared to inorganic zinc salts. Cell cultures of rat femoral-metaphyseal tissue treated with zinc and genistein produced a greater increase in BAP, deoxyribonucleic acid (DNA), and bone calcium content compared with either agent alone. Other studies have demonstrated that genistein and zinc produce synergistic effects on osteoclast apoptosis and bone mineralization. Animal studies support these findings by showing that the combination of zinc and genistein increases mineralization in bone over genistein alone. In both men and women, zinc was shown to potentiate the effect of high genistein-containing fermented food on bone markers by further increasing the levels of BAP and OC. Based on these data, genistein and zinc increase osteoblast activity while decreasing osteoclast activity to a greater extent than either genistein or zinc alone.

Trans-menaquinone-7 aids in the mineralization of bone by acting as a cofactor for gamma-carboxylase, an enzyme that substitutes carboxyl groups for glutamic acid (glutamyl) residues on a series of proteins collectively called Gla proteins. This carboxylation renders them physiologically active. Three Gla proteins have been identified in bone. Gla-osteocalcin (Gla-OC) residues bind calcium (Ca^2+) to be incorporated into hydroxyapatite crystals. Matrix Gla-protein forms a significant part of the structural matrix in bone into which the apatite is incorporated. Protein-S, a protein produced by osteoblasts and involved in bone remodeling homeostasis, is also vitamin K-dependent. In the absence of adequate vitamin K (or in the presence of warfarin), much of the OC remains uncarboxylated (un-OC) and Ca^2+ binding and deposition in bone is inadequate. Increased serum un-OC has been associated in humans with decreased BMD. Vitamin D3 and menaquinone-7 act synergistically on the molecular level to increase the production of OC, modulate the production of OPG, RANK and RANKL, and inhibit immature osteoclast differentiation.

Cholecalciferol

Cholecalciferol is converted in the body to calcitriol, the physiologically active form of vitamin D. Calcitriol regulates calcium and phosphate absorption and modulates serum calcium, renal calcium and phosphate excretion, bone formation and bone resorption. Vitamin D deficiency is associated with a negative calcium balance, increased parathyroid hormone levels, bone loss and increased risk of skeletal fracture. Severe deficiency results in hyperparathyroidism, hypophosphatemia, proximal muscle weakness, bone loss, and osteomalacia.

METABOLISM

CALCIUM COMPOUNDS

Calcium is absorbed most efficiently in separate doses of 500 mg or less. Upon dissociation in the stomach, calcium and phosphate are absorbed in the duodenum and proximal small intestine. Blood calcium levels are tightly regulated by parathyroid hormone (PTH) and calcitonin. PTH increases calcium blood concentration while decreasing phosphate concentrations. Calcitonin decreases serum calcium and phosphate levels in the blood. Therefore, the addition of phosphate with calcium is essential since both PTH and calcitonin can lead to decreases in phosphate, an essential component of bone. The combination of calcium and phosphate in Fosteum PLUS provides the proper balance for net bone building.

GENISTEIN AGLYCONE

The genistein in Fosteum PLUS is freely absorbed in the gut where it is at least partly converted to one metabolite, 7-O-beta-glucuronide, before it crosses the mucosa from the intestinal lumen. In hepatic first pass metabolism, genistein is converted via a two-stage process involving initial CYP450-mediated hydroxylation, followed by glucuronidation and sulfonation to the principal conjugated circulating metabolites. Genistein metabolites are converted back into the aglycone form in a variety of tissues. The aglycone is believed to be the principal active form, but conjugates have shown some activity in estrogen-receptor binding assays. Genistein and its conjugates are excreted via urine and bile.

TRANS-MENAQUINONE-7

Vitamin K occurs in two isomeric forms and several sub-isomers. Vitamin K2 (also known as menaquinone) has primary action on bone and vasculature. Vitamin K1 (also known as phylloquinone) exerts its primary action on the clotting sequence (thrombin, prothrombin). Vitamin K2 is present in meat, milk products, cheese, and eggs, while Vitamin K1 is found primarily in green leafy vegetables and vegetable oils. In the liver, menaquinone enters hepatocytes by endocytosis, binding to low density lipoprotein receptor (LDLR) and lipoprotein related receptors (LRP). Menaquinone is further combined with very low-density lipoprotein and excreted into the circulation. Circulating menaquinone-lipoprotein complexes bind to LDLR and LRP on the surface of osteoblasts in bone matrix to deliver menaquinone to bone building cells.

Citrated zinc bisglycinate consists of zinc chelated by glycine in the presence of citric acid. Once absorbed, the zinc is released from the chelate. Subsequently, glycine is utilized in normal protein metabolism and zinc is bound to albumin as well as blood cells and distributed throughout the body. The citrate is absorbed and utilized in the tricarboxylic acid cycle (Krebs cycle). The majority of zinc in the human body is found in muscle and bone. Excretion occurs predominantly via the feces.

CHOLECALCIFEROL

Ultraviolet light acts on 7-dehydrocholesterol (provitamin D3) in skin, where it is converted to 9,10-secosterol (previtamin D3). Previtamin D3 is converted into 25-hydroxycholecalciferol in the liver by the P450 enzyme CYP27. This molecule is further converted in the kidney by the P450 enzyme CYP27B1 to the active hormone, 1,25-dihydroxycholecalciferol (calcitriol). Vitamin D3 stimulates the absorption of both calcium and phosphate in the upper intestine.

CLINICAL EXPERIENCE

HEPATIC AND RENAL EFFECTS

In clinical studies, the effects of genistein on blood chemistries, including hepatic and renal function measures, were compared in post-menopausal subjects receiving genistein plus calcium carbonate (calcium) and vitamin D3 with post-menopausal, age-matched subjects receiving only calcium and vitamin D3. No change in laboratory values were noted over a three year period in either group and all measures remained within normal limits.

There are no known adverse hepatic or renal effects of menaquinone-7, citrated zinc bisglycinate or cholecalciferol.

EFFECTS ON REPRODUCTIVE TISSUES

Effects of the genistein in Fosteum PLUS on breast density, vaginal cytology and endometrial thickness were tested in long-term (3 years) double blind, placebo-controlled clinical trials. One trial with 30 post-menopausal subjects in each arm found that genistein did not affect endometrial thickness over a one year period compared to placebo. In other controlled trials, daily administration of 54 mg of genistein over one, two and three year periods produced no increases in endometrial thickness or breast density in post-menopausal women. Furthermore, a subset of 119 post-menopausal women showed no change in vaginal cytology following two years of daily genistein therapy. Genistein was shown to be equivalent in women with endometrial hyperplasia to norethisterone acetate for decreasing signs of bleeding, endometrial thickness and improving uterine cytology. These data suggest that the genistein in Fosteum PLUS does not produce adverse estrogenic effects in reproductive tissues.

CARDIOVASCULAR SAFETY

Dietary intake of calcium should be considered when dosing Fosteum PLUS, which contains 500 mg of dicalcium malate and pentacalcium hydroxide triphosphate per capsule (175 mg of elemental calcium). Post-menopausal women with bone loss should consume no more than 1,200 to 1,400 mg of elemental calcium per day. Excess calcium has recently been shown in observational studies to increase the risk of cardiovascular dysfunction, including myocardial infarction and stroke.

In a study of 60 post-menopausal subjects, the cardiovascular markers of those receiving the genistein in Fosteum PLUS were compared to a matched group receiving placebo. Homocysteine and C-reactive protein (CRP) were assessed at baseline and again at 6 months. No statistically significant differences were seen between groups. Soluble intercellular adhesion molecule-1 (ICAM), vascular cell adhesion molecule-1 (VCAM), fibrinogen and F2-isoprostane levels were assessed at baseline and again at 12 and 24 months in 389 post-menopausal subjects randomized to receive either genistein, calcium and vitamin D3 (product), or calcium and vitamin D3 only (placebo). At both 12 and 24 months, the levels of all four cardiovascular markers were reduced in the genistein group compared to both baseline and placebo at each time point. No significant changes in lipid profile were observed in either the genistein or the placebo group over the course of the study. These data indicate that genistein does not adversely affect markers of cardiovascular risk. An additional study of 53 post-menopausal women measured changes in flow-mediated vasodilation and plasma nitric oxide status. The genistein in Fosteum PLUS significantly increased plasma nitrite/nitrate levels and reduced levels of endothelin-1 compared to placebo. After 12 months of use, forearm blood flow increased significantly during reactive hyperemia in the genistein group compared to placebo. Flow-mediated dilation in the proximal and distal brachial arteries both increased significantly after genistein administration. The purified genistein in Fosteum PLUS improved endothelial function in a cohort of post-menopausal women. Finally, in post-menopausal women with metabolic syndrome (n=120), genistein in Fosteum PLUS was shown to statistically decrease LDL and triglycerides, while increasing HDL against placebo.

In large observational studies, menaquinone-7 was shown to reduce arterial calcium accumulation and protect against cardiovascular dysfunction. In the cardiovascular system, deficiency of carboxylated matrix Gla protein (MGP) is associated with arterial calcification and the progression of vascular disease. Menaquinone-7 increases the circulating concentrations of carboxylated MGP.

MENOPAUSAL SYMPTOMS

In three published studies with a combined enrollment of more than 300 post-menopausal women, the genistein in Fosteum PLUS progressively reduced the number of symptomatic vasomotor episodes by an average of more than 50% at the 24 month follow-up. In these studies, vasomotor symptoms were unchanged in the placebo groups.

BLOOD GLUCOSE AND INSULIN RESISTANCE

The genistein in Fosteum PLUS was also found to significantly reduce fasting glucose and insulin levels, as well as insulin resistance, in 198 post-menopausal women over a 2 year period and in a subset of 71 patients over a 3 year period when compared to placebo. In a separate study of post-menopausal women with metabolic syndrome (n=120), the genistein in Fosteum PLUS was statistically shown to decrease fasting blood glucose and insulin as well as insulin resistance versus placebo.

DRUG INTERACTIONS

CALCIUM COMPOUNDS

Thiazide diuretics inhibit renal calcium excretion. Care should be taken to monitor serum calcium in patients with high dietary calcium intake, and those who are taking both supplemental calcium and thiazides. Calcium can interfere with absorption of thyroid hormone. People taking thyroid medications should allow at least one hour between doses of thyroid medications and Fosteum Plus.

GENISTEIN AGLYCONE

The genistein in Fosteum PLUS was tested in in vitro pooled human liver microsome assays for CYP1A2, 2A6, 2C8, 2C9, 2D6, and 3A4. Inhibition of the 1A2, 2A6, 2D6 and 3A4 isozymes was low, however, inhibition of CYP450 2C8 and 2C9 was observed with IC50s of 2.5 and 2.8 μM, respectively. Results from a steady-state pharmacokinetic study in post-menopausal women showed that the level of circulating genistein was in the low nanomolar range and undetectable at most time points in many subjects. These data suggest that circulating genistein does not reach the concentration required to produce any clinically significant interactions with co-administered drugs. The effects of the principal circulating metabolites of genistein on CYP450-mediated metabolism are currently unknown.

TRANS-MENAQUINONE-7

Warfarin specifically antagonizes the carboxylation of Gla proteins thus rendering them inactive. Warfarin therapy is associated with prolongation of the clotting sequence (usually measured by a prothrombin time and International Normalized Ratio or INR). Warfarin therapy is also associated with the development of osteopenia/osteoporosis and arterial calcification. The specific and rapidly acting antidote for bleeding associated with warfarin overdose is Vitamin K1 (phylloquinone) by parental administration. In a study of young, healthy anti-coagulated patients on warfarin, addition of vitamin K2 (menaquinone-7) resulted in a decrease in INR. There are no other known drug interactions for menaquinone-7. See precautions for recommendations regarding use in patients taking warfarin.

CHOLECALCIFEROL

Cimetidine, thiazides and anticonvulsants may increase catabolism of vitamin D3. Cholestyramine and other bile acid sequestrants, as well as mineral oil, orlistat and olestra may impede absorption of vitamin D3 from the intestine.

TOXICITY

CALCIUM AND PHOSPHATE COMPOUNDS

Dietary intake of calcium should be considered when dosing Fosteum PLUS, which contains 350 mg of total elemental calcium when taken twice daily. Post-menopausal women with bone loss should consume no more than 1,200 to 1,400 mg of elemental calcium per day from all sources. Recent studies have shown that excess calcium can increase the risk of myocardial infarction and stroke.

Dicalcium malate and pentacalcium hydroxide triphosphate in Fosteum PLUS have no known adverse hepatic effects. Patients with renal insufficiency have been shown to retain phosphate, which can lead to hyperphosphatemia which, in turn, may result in hypocalcemia due to precipitation of phosphate with the calcium in multiple tissues. Ectopic calcification, secondary hyperparathyroidism and renal osteodystrophy can occur in patients with renal insufficiency who consume both calcium and phosphate.

GENISTEIN AGLYCONE

Genistein showed no toxicity in rats following acute dosing up to 2000 mg/kg. Long-term toxicity studies up to 52 weeks duration using oral administration of 0-500 mg/kg/day in rats and dogs showed minimal adverse effects. From these studies, the no observed adverse effect level (NOAEL) for genistein in rats was determined to be 50 mg/kg/day and in dogs >500 mg/kg/day. These intake levels are at least 50-foldgreater than the recommended human dose of the genistein in Fosteum PLUS on a mg/kg basis.

ZINC (ELEMENTAL)

The National Academy of Sciences (NAS) upper acceptable limit for self-administration is 40 mg/day of elemental zinc, the equivalent of ten Fosteum PLUS capsules per day. Zinc is considered acutely toxic at 200 mg elemental zinc per day, the equivalent of 50 Fosteum PLUS capsules.

CHOLECALCIFEROL

Cholecalciferol may produce toxicity with long term, high-dose consumption. While medical doses of vitamin D3 up to 10,000 IU per day are sometimes administered under physician supervision, the upper acceptable limit for self-administration is 2,000 IU per day according to the Daily Reference Intakes (DRI) of the Institute of Medicine published by the NAS in 2004. Signs and symptoms of vitamin D toxicity include hypercalcemia, hypercalciuria, anorexia, nausea, vomiting, polyuria, polydipsia, weakness and lethargy. Serum and urine calcium levels should be monitored in patients with suspected vitamin D toxicity, and therapy initiated promptly in symptomatic patients

SPECIAL POPULATIONS

PREGNANT OR NURSING WOMEN

Fosteum PLUS has not been tested in pregnant or nursing women.

MALES

Fosteum PLUS has not been studied for its effect on bone in human males. No specific studies on genistein aglycone and feminization in human males exist.

PEDIATRICS

Fosteum PLUS has not been tested in pediatric patients.

INDICATIONS AND USAGE

INDICATIONS

Fosteum PLUS is indicated for the clinical dietary management of the metabolic processes of osteopenia and osteoporosis.

USAGE

Fosteum PLUS may be taken with additional calcium and/or vitamin D3 if directed by a physician after determining dietary intake of both nutrients. In clinical trials of the genistein (54 mg/day) used in Fosteum PLUS, patients received 1,000 mg of calcium carbonate and 800 IU vitamin D3 per day in two divided doses. See Dosage and Administration for additional information.

INTERACTIONS WITH FOOD

Fosteum PLUS can be taken with or without other foods. Fosteum PLUS may be taken with any beverage desired.

PRECAUTIONS AND CONTRAINDICATIONS

GENERAL

Causes of osteopenia or osteoporosis other than menopause or aging should be considered.

HYPERSENSITIVITY

Fosteum PLUS is contraindicated for anyone having a hypersensitivity to any ingredient in the product.

PATIENTS WITH CANCER

Fosteum PLUS has not been specifically studied in patients with a history of cancer of the breast or reproductive organs. Major studies on isoflavone intake have been published including one epidemiological study involving 18,312 postmenopausal women who were followed for an average of 9.2 years. Based on these findings, Fosteum PLUS may be suitable for the management of osteopenia and osteoporosis in these populations. The decision to use Fosteum PLUS in these clinical situations should be made in consultation with the patient’s physician.

VITAMIN D DEFICIENCY / OVERPRODUCTION

Fosteum PLUS is not intended to treat vitamin D3 deficiency, generally characterized in the literature by serum levels of 25-hydroxycholecalciferol below 9 ng/mL.

In patients suffering from diseases associated with unregulated overproduction of calcitriol, supplemental vitamin D3 may worsen hypercalcemia and/or hypercalciuria. Therefore, Fosteum PLUS is not recommended in these patients.

PREGNANCY

Animal studies suggest that genistein may produce developmental abnormalities of the male and female genital tracts if consumed during early stages of pregnancy. Effects in infants of nursing mothers are uncertain. Therefore, Fosteum PLUS is not recommended in pregnant and lactating women. Women capable of becoming pregnant should use appropriate contraception when taking Fosteum PLUS. The genistein in Fosteum PLUS has not been tested in women capable of becoming pregnant.

WARFARINIZED PATIENTS

Vitamin K1(phylloquinone) is a specific antagonist of warfarin on the Gla proteins of the clotting system. Vitamin K2 (menaquinone) has similar, but weaker, effects on these proteins. The few published studies available suggest that doses of 300 μg/day may be required for clinically significant warfarin antagonism to occur, but these data vary greatly depending on individual dietary intake of vitamin K containing foods. Primus recommends that patients taking warfarin should NOT use Fosteum PLUS. However, if a physician feels that the use of Fosteum PLUS is indicated, the INR should be followed very carefully, probably at least twice weekly, and warfarin dose adjustments made as required until the INR is stabilized. The patient should also be given dietary advice to avoid high vitamin K containing foods and be advised not to alter or miss a dose of Fosteum PLUS. If a dose alteration is unavoidable, the patient should promptly see the physician for repeat monitoring.

ADVERSE EVENTS

CALCIUM COMPOUNDS

Neither dicalcium malate nor pentacalcium hydroxide triphosphate are known to cause specific adverse events. All calcium can be constipating, especially if used in excess. Proper hydration is recommended with any calcium-containing product.

GENISTEIN AGLYCONE

In a three-year clinical trial, 389 subjects were randomized to either genistein plus calcium and vitamin D3 n=198, or calcium and vitamin D3 alone n=191. A total of 52 subjects in both groups discontinued due to adverse events. Study discontinuation in these subjects was due to gastrointestinal symptoms, including abdominal and epigastric pain, dyspepsia, vomiting and constipation. Discontinuation was reported in both groups. The incidence of adverse events was statistically higher in the genistein group throughout the study. The major adverse events are shown in the table below without attribution of causality.

Adverse Events | Year 1 |  | Year 2 |  | Year 3
Adverse Events | Genistein+Ca/D3; (n=178) | Ca/D3; (n=172) | Genistein+Ca/D3; (n=150) | Ca/D3; (n=154) | Genistein+Ca/D3; (n=71) | Ca/D3; (n=67)
Abdominal Pain | 4 (2.2%) | 2 (1.1%) | 2 (1.3%) | 1 (0.6%) | 1(1.4%) | 1(1.5%)
Dyspepsia | 2 (1.1%) | 1 (0.6%) | 7 (4.7%) | 2 (1.3%) | 2(2.8%) | 1(1.5%)
Constipation | 5 (2.8%) | 3 (1.7%) | 8 (5.3%) | 3 (1.9%) | 2(2.8%) | 1(1.5%)

Some of these adverse event occurrences may be attributable to the intake of 1,000 mg per day of calcium carbonate by subjects in both groups. Taking Fosteum PLUS with food may reduce or eliminate some gastrointestinal symptoms.

TRANS-MENAQUINONE-7

In clinical studies of menaquinone-7, adverse events have been similar to placebo. Small increases in coagulation test values compared to placebo were noted, although these values remained within normal ranges.

PHARMACOKINETICS

GENISTEIN AGLYCONE

To determine the disposition of the genistein in Fosteum PLUS, a steady-state pharmacokinetic (PK) study was conducted in post-menopausal women aged 50-66. Ten subjects took genistein without food (fasted group) and 10 subjects took genistein with food (fed group) twice daily (54 mg total) for seven (7) days. On the eighth day, blood was collected at 1, 2, 3, 4, 6, 8, 10, 12, 24, 36, 48 and 96 hours after ingesting genistein with (fed group) or without (fasted group) food. Concentrations of serum aglycone (protein bound and unbound) and total genistein (aglycone plus circulating conjugated forms) were determined at each time point for standard pharmacokinetic analyses.

Levels of free genistein aglycone were in the low nanomolar range and below the level of quantification in several subjects. Therefore, meaningful pharmacokinetic parameters could not be calculated from the data. Consistent with previous studies, the majority of circulating genistein existed in the conjugated form. Pharmacokinetic analyses for total genistein reported in the table below revealed no significant difference in any parameter between the fed and fasted groups, suggesting that Fosteum PLUS may be taken with or without food. The serum half-life (t1/2) among all subjects was 9.6 hours. Based on this profile, BID dosing is recommended.

Prandial State | N | Total Genistein | Mean ±SD
Fasting | 10 | Cmax (ng/mL); Tmax (hours); T1/2 (hours); AUC | 837.5 ± 414.8; 2.0 ± 1.2; 8.1 ± 4.9; 9622.8 ± 5843.0
Fed | 9 | Cmax (ng/mL); Tmax (hours); T1/2 (hours); AUC | 671.1 ± 297.1; 3.3 ± 1.5; 11.2 ± 3.6; 11045.2 ± 6208.6

TRANS-MENAQUINONE-7

A single-dose pharmacokinetic study demonstrated that menaquinone-7 is well absorbed with a maximal serum concentration (Tmax) at 6 hrs. A separate single-dose pharmacokinetic study showed a Tmax at 4 hrs. Both studies showed a biphasic depletion of menaquinone-7 with half of the molecule excreted in approximately 10 hours, but not reaching baseline for 3 days. Half-life (T1/2) estimations are difficult to calculate due to the biphasic kinetics.

CLINICAL STUDIES

DIETARY MANAGEMENT OF OSTEOPENIA AND OSTEOPOROSIS

Effect on Bone Mineral Density

Efficacy of the genistein in Fosteum PLUS was demonstrated in a multi-center, double-blind, placebo-controlled clinical study of 389 randomized post-menopausal patients with osteopenia or osteoporosis (genistein n=198; placebo n=191). All subjects received calcium (1,000 mg/day) and vitamin D3 (800 IU/day) in two divided doses.

Mean Percent Change in BMD over 24 Months

SITE | 12 months vs. baseline |  | 24 months vs. baseline
SITE | Genistein +Ca/D3 (n=178) | Ca/D3 (n=172) | Genistein +Ca/D3 (n=150) | Ca/D3 (n=154)
Femoral Neck | 2.4% | -2.2% | 5.1% | -5.3%
Lumbar Spine | 2.9% | -3.6% | 5.8% | -6.3%

After two years, both lumbar spine and femoral neck showed significant increases in BMD relative to both baseline and placebo in patients who received genistein. In a third year extension, 138 patients continued on blinded study product. Patients taking the genistein in Fosteum PLUS showed a continued increase in BMD at both lumbar spine and femoral neck. In this cohort, 85% of the patients in the genistein arm showed increased BMD.

Mean Percent Change in BMD over 24 and 36 Months (Extended Study Group)

SITE | 24 months vs. baseline |  | 36 months vs. baseline
SITE | Genistein +Ca/D3 (n=71) | Ca/D3 (n=67) | Genistein +Ca/D3 (n=71) | Ca/D3 (n=67)
Femoral Neck | 5.2% | -5.4% | 7.0% | -7.5%
Lumbar Spine | 7.3% | -6.3% | 10.3% | -10.6%

Measurement of bone markers supported the proposed mechanism of action. Levels of formation markers were increased, and levels of resorption markers were reduced in the genistein group compared with baseline as shown in the table below.

Mean Percent Change in Bone Markers at 12, 24 and 36 Months vs. Baseline

 | 12 months vs. baseline |  | 24 months vs. baseline |  | 36 months vs. baseline
 | Genistein + Ca/D3 (N=178) | Ca/D3 (N=172) | Genistein + Ca/D3 (N=150) | Ca/D3 (N=154) | Genistein + Ca/D3 (N=71) | Ca/D3 (N=67)
BAP | +32.7% | -0.8% | +38.5% | -1.1% | +45.3% | -1.2%
IGF-1 | +18.0% | -2.3% | +13.0% | +1.6% | +16.7% | -3.0%
PYR | -14.5% | -3.3% | -13.5% | -1.0% | -15.8% | -2.8%
DPYR | -12.4% | -1.2% | -10.2% | -0.9% | -14.1% | -3.0%
CTX | -24.9% | +2.3% | -35.5% | +2.9% | -43.7% | +6.2%

Genistein’s efficacy was also shown in a one year trial of 90 osteopenic or osteoporotic, post-menopausal subjects vs. placebo and vs. hormone replacement therapy (HRT). Baseline values were matched for all parameters. The BMD values at 12 months are shown in the table below:

Mean Percent Change in BMD at 12 Months vs. Baseline

SITE | GENISTEIN (n=30) | HRT (n=30) | PLACEBO (n=30)
Femoral Neck | 3.6% | 2.4% | -0.7%
Ward’s Triangle | 4.0% | 3.0% | -0.4%
Lumbar Spine | 3.0% | 3.8% | -1.6%

TRANS-MENAQUINONE-7

In large epidemiological studies, low serum K2 levels have been associated with increased risk of low bone mass and osteoporotic fractures. In a study, 94 osteoporotic postmenopausal women treated with HRT for >1year, were started on menaquinone. In 84 of the patients, BMD increased by 2.9% after 1 year, and reached and maintained a plateau of 5.4% increase (+/-1.2%) after 3 years. In the remaining 10 patients, BMD fell slightly after reaching a plateau. Multiple other studies have shown improvement of markers of bone metabolism with vitamin K2 administration, and these findings were reflected in improvements in BMD and fracture rates. Other studies have suggested that vitamin K2 improves bone quality independent of its effects on BMD.

Numerous epidemiological and interventional studies have demonstrated that vitamin MK-7 increases bone and plasma levels of the active (carboxylated) form of osteocalcin, increases bone mineral content (BMC) and, to a lesser extent, bone mineral density (BMD) and bone strength. Uncarboxylated osteocalcin (un-OC) levels have been shown to positively correlate with fracture risk. In one study of 195 women aged 70-101 years, 23% were found to have elevated levels of un-OC. 15 of which suffered a hip fracture in an 18 month follow-up period giving a relative risk of 5.9. Review articles and other reports, including a prospective longitudinal study of 7598 elderly women have demonstrated reduction in fracture risk independent of BMD suggesting MK-7improves structural bone quality. A 3 year randomized trial of 120 postmenopausal women treated with 180 mcg MK-7 daily vs.124 placebo treated women (published in 2013) found reduction of plasma un-OC of 58% in those given MK-7 vs. 4% in the placebo group. After 3 years the MK-7 treated group had significantly less bone loss in the femoral neck (p=0.023 for BMC and p=0.014 for BMD) and lumbar spine (p=0.001 for BMC and 0.111 for BMD). In the MK-7 group there was less loss of vertebral height in T10-12 (p=0.003) although no differences were seen in T7-9 and L1-3. One (1) clinical fracture occurred in the MK-7 treated women and 6 in the placebo group.

TRANS-MENAQUINONE-7 AND CORTICOSTERIOD-INDUCED BONE LOSS

In a short-term study (10 wks) of 20 patients, menaquinone halted prednisolone-induced loss of BMD in patients taking both trans-menaquinone-7 and prednisolone.

FRACTURE DATA

The studies performed on the genistein in Fosteum PLUS to date were not intended to assess new incident fractures. These studies showed reduced markers of bone resorption, increased markers of bone formation and increased BMD in clinical trials. Anecdotally, in the 389 patient clinical trial comparing genistein to placebo over a three-year period, there were three fractures of the sacrum in the placebo (calcium and
vitamin D3) group while no fractures were observed in the genistein group. Studies in animals have demonstrated an increase in bone quality including an increase in bone breaking strength and improvement in architecture on histological examination after genistein administration. In epidemiological studies of populations with high serum concentrations of genistein and menaquinone, there is a large reduction in the observance of fracture when compared with populations demonstrating low concentrations of genistein and menaquinone. No specific clinical trials using fracture as an endpoint have been performed on either the genistein or the menaquinone-7 in Fosteum PLUS as the reported data on fracture came from food-based studies.

OVER USAGE

CALCIUM COMPOUNDS

Supplemental calcium should be administered with caution in patients with high bone turnover states, such as Paget’s disease, and in patients with a history of calcium containing urolithiasis, hyperparathyroidism and certain renal tubular abnormalities.

GENISTEIN AGLYCONE

There are no known cases of over usage of the genistein in Fosteum PLUS. Animal studies have shown that consuming the equivalent of 75 Fosteum PLUS capsules at one time did not produce adverse events. If an over usage were to occur, patients should be managed by systematic and supportive care as soon as possible following product consumption.

TRANS-MENAQUINONE-7

There are no known cases of over usage of the trans-menaquinone-7 in Fosteum PLUS. The ‘no observed adverse effect level’ (NOAEL) of menaquinone-7 administered orally in rats for 90 days was 10 mg/kg body weight/day. For a 60 kg human (132 lbs.), this is more than 300 times the dose present in a Fosteum PLUS capsule. If an over usage were to occur, patients should be managed by systematic and supportive care as soon as possible following product consumption.

ZINC (ELEMENTAL)

Zinc is considered acutely toxic at 200 mg elemental zinc per day, the equivalent of 50 Fosteum PLUS capsules. Those taking high doses of zinc-containing vitamins, cold medications, such as zinc lozenges, and some ophthalmic supplements for retinal diseases, should be monitored for zinc and copper status.

CHOLECALCIFEROL

There is limited information regarding acute vitamin D3 toxicity in humans. The recommended upper limit for self-administration of cholecalciferol is 2,000 IU per day. Symptoms of vitamin D toxicity include hypercalcemia, hypercalciuria, anorexia, nausea, vomiting, polyuria, polydipsia, weakness and lethargy. Serum and urine calcium levels should be monitored in patients with suspected vitamin D toxicity.

DOSAGE AND ADMINISTRATION

Fosteum PLUS should be taken twice a day, approximately 12 hours apart, and may be taken with or without food. Fosteum PLUS has no food limitations. There are no postural limitations.

HOW SUPPLIED

Fosteum PLUS is a green and white capsule with “FOSTEUM PLUS” and “52011” printed on the body of the capsule.

They are supplied as follows:

68040-611-16 unit-of-use bottle of 60 capsules with desiccant (30-day supply)

68040-611-08 carton of 1 5-day sample blister pack (10 capsules total)

Storage

Store at room temperature 59°– 86°F (15°– 30°C). Protect from light and moisture. Store capsules in original bottle until usage. Keep out of reach of children.

Manufactured for:
Primus Pharmaceuticals, Inc.
Scottsdale, AZ 85253
www.primusrx.com

U.S. Patent Nos. 7,582,418*, 7,838,042*, 8,338,393, 9,066,921, 9,486,438, WO2009063485, WO2010103545, WO2012059942. Patents pending. *Used under license from Albion Laboratories, Inc., Clearfield, UT.

©2020 Primus Pharmaceuticals, Inc. All rights reserved. 13506-1020

PRINCIPAL DISPLAY PANEL

68040-611-16

Dispensed by Prescription

Fosteum® PLUS

Calcium compounds (dicalcium malate + pentacalcium hydroxide triphosphate) (500 mg)/phosphate (70 mg)
genistein aglycone (27 mg)/citrated zinc bisglycinate (20mg)
trans-menaquinone-7 (90 μg)/cholecalciferol (400 IU)

MEDICAL FOOD PRODUCT

For the Clinical Dietary Management of the Metabolic Processes of Osteopenia and Osteoporosis

CONTENTS: 60 CAPSULES